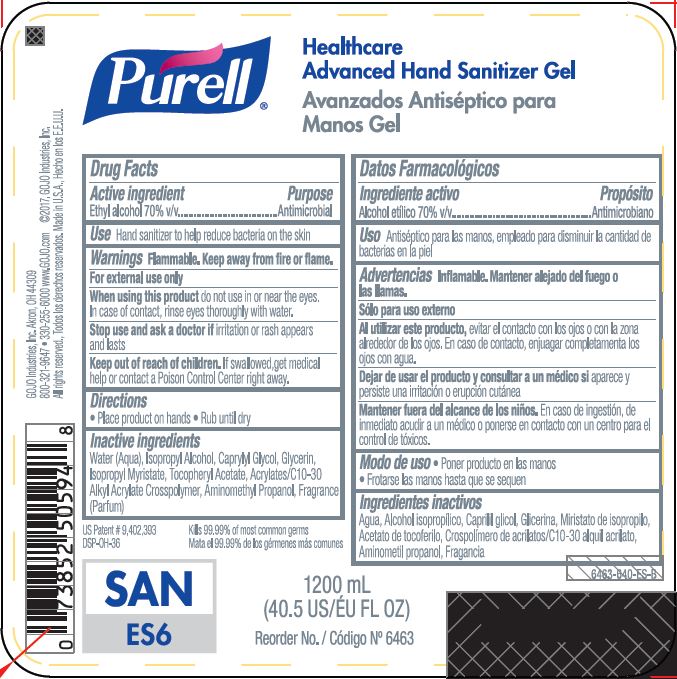 DRUG LABEL: PURELL Healthcare Advanced Hand Sanitizer Gel
NDC: 21749-716 | Form: GEL
Manufacturer: GOJO Industries, Inc.
Category: otc | Type: HUMAN OTC DRUG LABEL
Date: 20241211

ACTIVE INGREDIENTS: ALCOHOL 0.7 mL/1 mL
INACTIVE INGREDIENTS: WATER; ISOPROPYL ALCOHOL; CAPRYLYL GLYCOL; GLYCERIN; ISOPROPYL MYRISTATE; .ALPHA.-TOCOPHEROL ACETATE, D-; AMINOMETHYLPROPANOL

PURELL Healthcare Advanced Hand Sanitizer Gel

Active ingredient

Ethyl alcohol 70% v/v

Purpose

Antimicrobial

Uses

- Hand sanitizer to help reduce bacteria on the skin

Warnings

Flammable. Keep away from fire or flame.

For external use only

WHEN USING

When using this productdo not use in or near the eyes. In case of contact, rinse eyes thoroughly with water.

Stop use and ask a doctor if irritation or rash appears and lasts

Keep Out of Reach of Children. If swallowed, get medical help or contact a Poison Control Center right away.

Directions

- Place product on hands
- Rub until dry

Inactive ingredients

Water (Aqua), Isopropyl Alcohol, Caprylyl Glycol, Glycerin, Isopropyl Myristate, Tocopheryl Acetate, Acrylates/C10-30 Alkyl Acrylate Crosspolymer, Aminomethyl Propanol, Fragrance (Parfum)